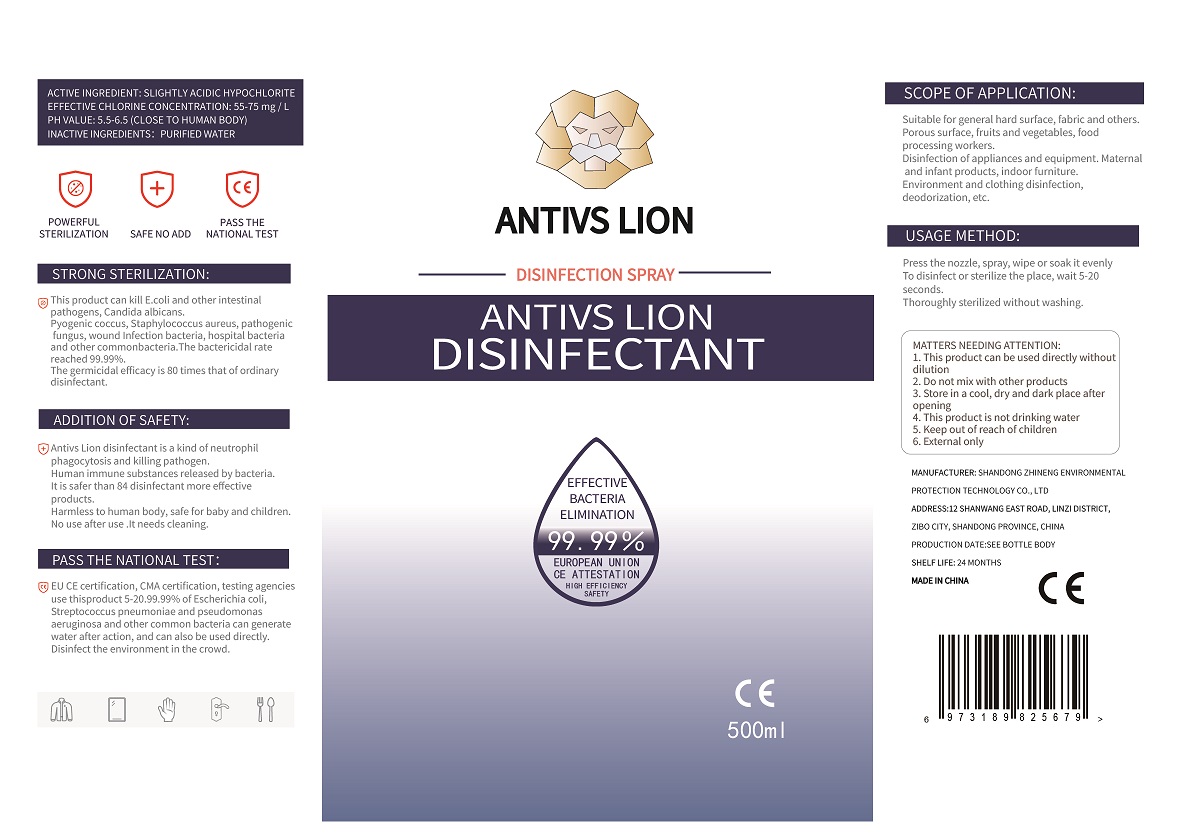 DRUG LABEL: Huoting slight acid hypochlorite disinfectant
NDC: 77688-101 | Form: LIQUID
Manufacturer: Shandong Zhineng Environmental Protection Technology Co., Ltd
Category: otc | Type: HUMAN OTC DRUG LABEL
Date: 20200521

ACTIVE INGREDIENTS: HYPOCHLOROUS ACID 100 mg/500 mL
INACTIVE INGREDIENTS: WATER

Zhineng, Disinfectant, Liquid-Spray, 500mL

Active Ingredient(s)

Slight acid hypochlorite 200 mg/L. Purpose: Kill microorganism.

Purpose

This product can kill E.coli and other intestinal pathogens, Candida albicans.

Pyogenic coccus, Staphylococcus aureus, pathogenic fungus, wound infection bacteria and other common bacteria.

Use

Suitable for general hard surface, fabric and others.

Porous surface, fruits and vegetables, food processing workers.

Disinfection of appliances and equipment.

Maternal and infant products, indoor furniture.

Environment and cloting disinfection, deoorization, etc.

Warnings

- Do not mix it with other products
- This product is not drinking water
- External only

Do not use

- on open skin wounds
- mixing this product with other disinfectants

When using this product keep out of eyes, ears, and mouth.

In case of contact with eyes, rinse eyes thoroughly with water.

This product is for external use only. It is not drinking water.

Do not mix this product with other products.

No use after use. It needs cleaning.

Stop use and ask a doctor if irritation or rash occurs. These may be signs of a serious condition.

Keep out of reach of children.

Directions

Press the nozzle, spray, wipe or soak it evenly.

To disinfect or sterilize the place, wait 5-20 seconds.

Thoroughly sterilized without washing.

Other information

Store in a cool, dry and dark place after opening.

Inactive ingredients

Water.